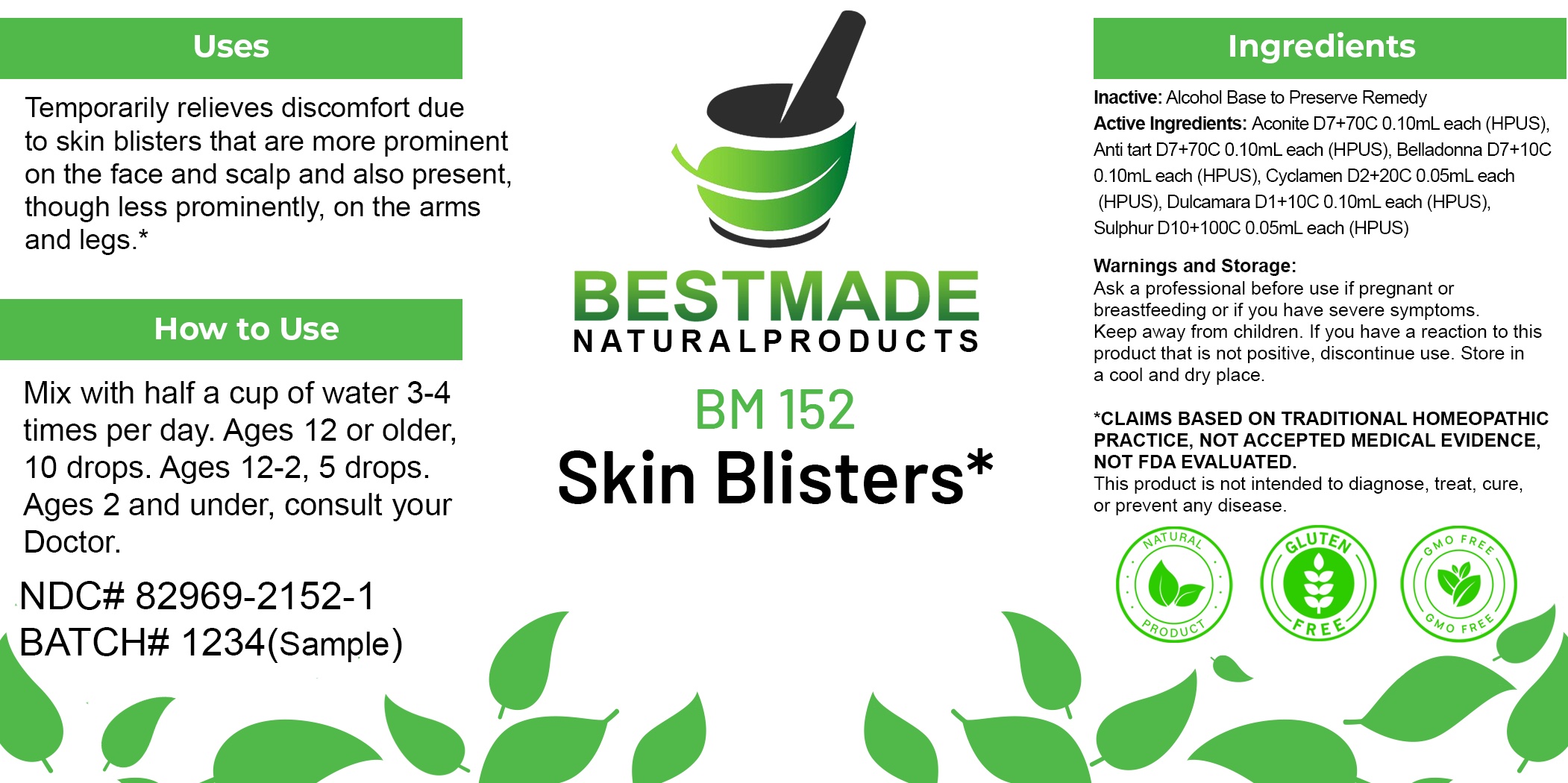 DRUG LABEL: Bestmade Natural Products BM152
NDC: 82969-2152 | Form: LIQUID
Manufacturer: Bestmade Natural Products
Category: homeopathic | Type: HUMAN OTC DRUG LABEL
Date: 20250218

ACTIVE INGREDIENTS: SOLANUM DULCAMARA FLOWER 30 [hp_C]/30 [hp_C]; ACONITUM NAPELLUS WHOLE 30 [hp_C]/30 [hp_C]; ANTIMONY POTASSIUM TARTRATE 30 [hp_C]/30 [hp_C]; ATROPA BELLADONNA 30 [hp_C]/30 [hp_C]; SULFUR 30 [hp_C]/30 [hp_C]; CYCLAMEN PURPURASCENS TUBER 30 [hp_C]/30 [hp_C]
INACTIVE INGREDIENTS: ALCOHOL 30 [hp_C]/30 [hp_C]

BM152

DOSAGE AND ADMINISTRATION

How to Use

Mix with half a cup of water 3-4 times per day. Ages 12 or older, 10 drops. Ages 12-2, 5 drops. Ages 2 and under, consult your Doctor.

Inactive:

Alcohol Base to Preserve Product

Active Ingredients:

Aconite D7+70C 0.10mL each (HPUS), Anti tart D7+70C 0.10mL each (HPUS), Belladonna D7+10C 0.10mL each (HPUS), Cyclamen D2+20C 0.05mL each (HPUS), Dulcamara D1+10C 0.10mL each (HPUS), Sulphur D10+100C 0.05mL each (HPUS)

Uses
Temporarily relieves discomfort due to skin blisters that are more prominent on the face and scalp and also present, though less prominently, on the arms and legs.*

Uses
Temporarily relieves discomfort due to skin blisters that are more prominent on the face and scalp and also present, though less prominently, on the arms and legs.*

KEEP OUT OF REACH OF CHILDREN

Warnings and Storage:

Ask a professional before use if pregnant or breastfeeding or if you have severe symptoms.

Keep away from children. If you have a reaction to this product that is not positive, discontinue use. Store in a cool and dry place

*CLAIMS BASED ON TRADITIONAL HOMEOPATHIC PRACTICE, NOT ACCEPTED MEDICAL EVIDENCE NOT FDA EVALUATED.
This product is not intended to diagnose, treat, cure, or prevent any disease.

Warnings and Storage:

Ask a professional before use if pregnant or breastfeeding or if you have severe symptoms.

Keep away from children. If you have a reaction to this product that is not positive, discontinue use. Store in a cool and dry place

*CLAIMS BASED ON TRADITIONAL HOMEOPATHIC PRACTICE, NOT ACCEPTED MEDICAL EVIDENCE NOT FDA EVALUATED.
This product is not intended to diagnose, treat, cure, or prevent any disease.

Entire package label